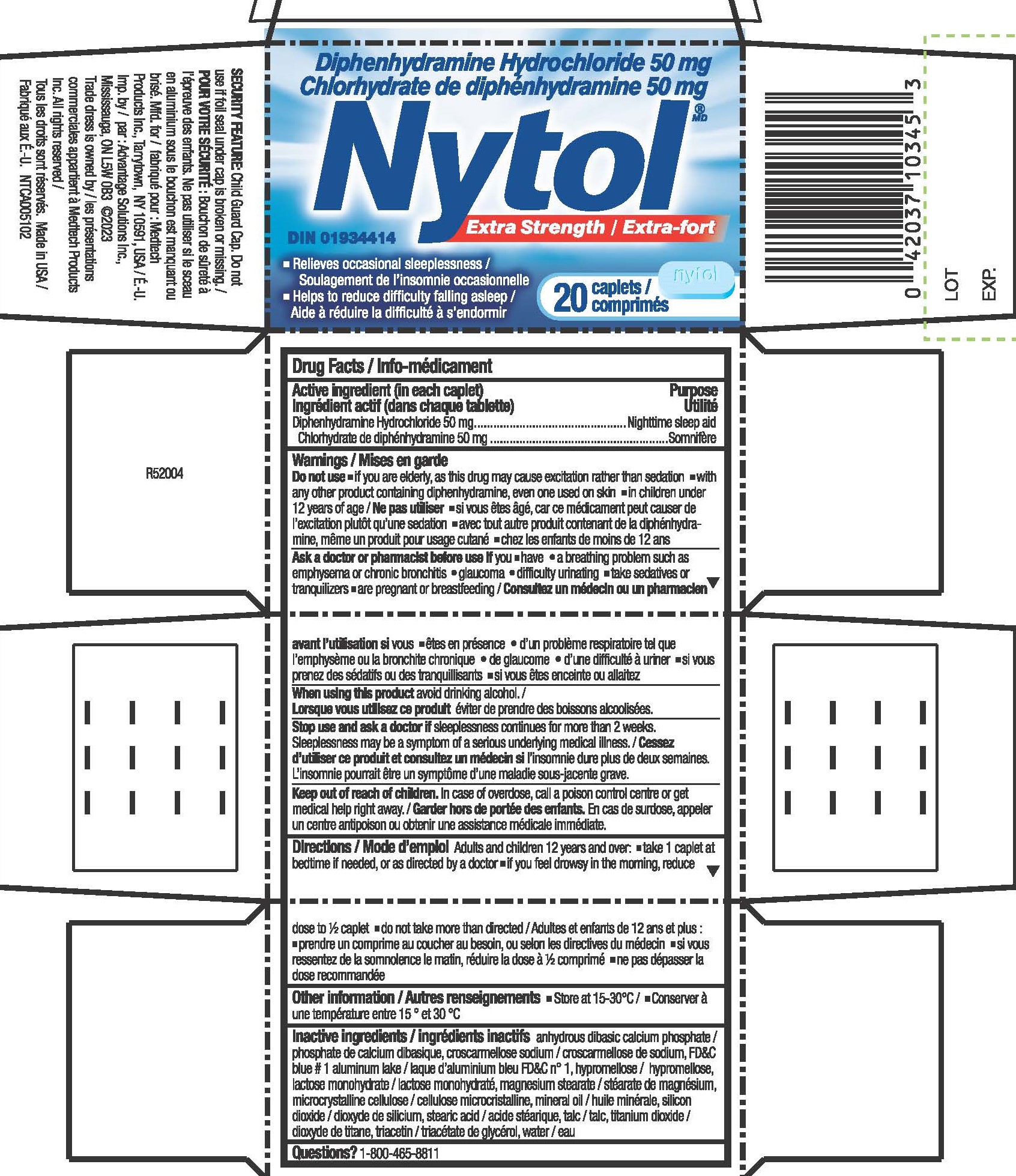 DRUG LABEL: Diphenhydramine Hydrochloride
NDC: 10267-4380 | Form: TABLET, FILM COATED
Manufacturer: Contract Pharmacal Corp.
Category: otc | Type: HUMAN OTC DRUG LABEL
Date: 20240506

ACTIVE INGREDIENTS: DIPHENHYDRAMINE HYDROCHLORIDE 50 mg/1 1
INACTIVE INGREDIENTS: LIGHT MINERAL OIL; SILICON DIOXIDE; TRIACETIN; HYPROMELLOSES; MAGNESIUM STEARATE; MICROCRYSTALLINE CELLULOSE; STEARIC ACID; TALC; TITANIUM DIOXIDE; FD&C BLUE NO. 1; CROSCARMELLOSE SODIUM; DIBASIC CALCIUM PHOSPHATE DIHYDRATE; LACTOSE MONOHYDRATE

4380- Export